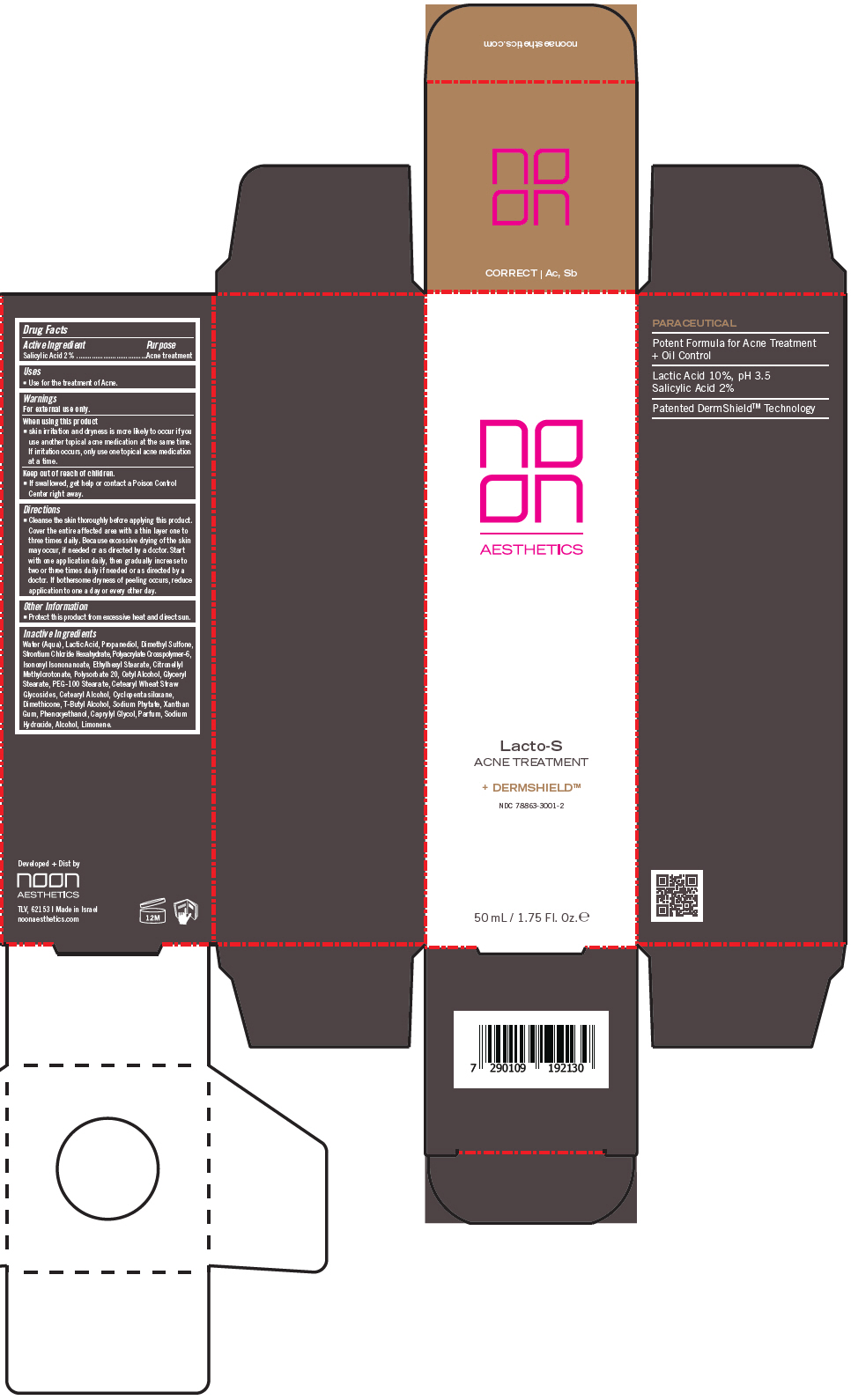 DRUG LABEL: LACTO-S 
NDC: 78863-3001 | Form: CREAM
Manufacturer: Noon Aesthetics M.R. Ltd
Category: otc | Type: HUMAN OTC DRUG LABEL
Date: 20240531

ACTIVE INGREDIENTS: SALICYLIC ACID 200 mg/1 mL
INACTIVE INGREDIENTS: WATER; LACTIC ACID, UNSPECIFIED FORM; DIMETHYL SULFONE; STRONTIUM CHLORIDE HEXAHYDRATE; POLYACRYLIC ACID (450000 MW); ISONONYL ISONONANOATE; ETHYLHEXYL STEARATE; CITRONELLYL METHYLCROTONATE; POLYSORBATE 20; CETYL ALCOHOL; GLYCERYL STEARATE SE; PEG-100 STEARATE; CETEARYL WHEAT STRAW GLYCOSIDES; CETOSTEARYL ALCOHOL; CYCLOMETHICONE 5; DIMETHICONE; TERT-BUTYL ALCOHOL; PHYTATE PERSODIUM; XANTHAN GUM; PHENOXYETHANOL; CAPRYLYL GLYCOL; FRAGRANCE 13576; SODIUM HYDROXIDE; ALCOHOL; LIMONENE, (+/-)-

LACTO-S
ACNE TREATMENT

Drug Facts

Active Ingredient

Salicylic Acid 2%

Purpose

Acne treatment

Uses

- Use for the treatment of Acne.

Warnings

For external use only.

When using this product

- skin irritation and dryness is more likely to occur if you use another topical acne medication at the same time. If irritation occurs, only use one topical acne medication at a time.

Keep out of reach of children.

- If swallowed, get help or contact a Poison Control Center right away.

Directions

- Cleanse the skin thoroughly before applying this product. Cover the entire affected area with a thin layer one to three times daily. Because excessive drying of the skin may occur, if needed or as directed by a doctor. Start with one application daily, then gradually increase to two or three times daily if needed or as directed by a doctor. If bothersome dryness of peeling occurs, reduce application to one a day or every other day.

Other Information

- Protect this product from excessive heat and direct sun.

Inactive Ingredients

Water (Aqua), Lactic Acid, Propanediol, Dimethyl Sulfone, Strontium Chloride Hexahydrate, Polyacrylate Crosspolymer-6, Isononyl Isononanoate, Ethylhexyl Stearate, Citronellyl Methylcrotonate, Polysorbate 20, Cetyl Alcohol, Glyceryl Stearate, PEG-100 Stearate, Cetearyl Wheat Straw Glycosides, Cetearyl Alcohol, Cyclopentasiloxane, Dimethicone, T-Butyl Alcohol, Sodium Phytate, Xanthan Gum, Phenoxyethanol, Caprylyl Glycol, Parfum, Sodium Hydroxide, Alcohol, Limonene.

Developed + Dist by
noon
AESTHETICS
TLV, 62153 | Made in Israel
noonaesthetics.com

PRINCIPAL DISPLAY PANEL - 50 mL Bottle Carton

no
on
AESTHETICS

Lacto-S
ACNE TREATMENT

+ DERMSHIELD™

NDC 78863-3001-2

50 mL / 1.75 Fl. Oz. ℮